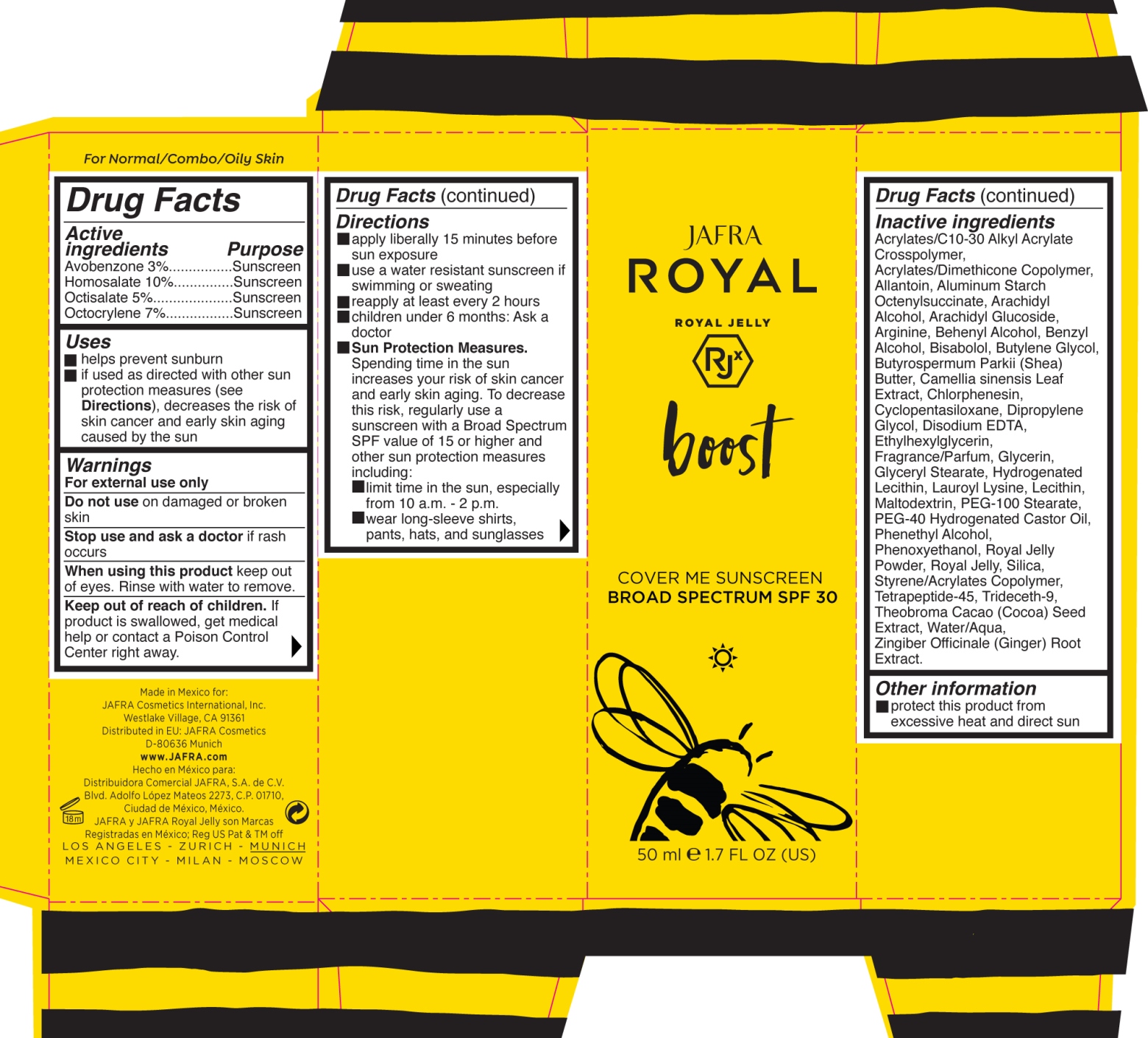 DRUG LABEL: Cover Me Sunscreen
NDC: 68828-280 | Form: LOTION
Manufacturer: Jafra Cosmetics International
Category: otc | Type: HUMAN OTC DRUG LABEL
Date: 20200611

ACTIVE INGREDIENTS: AVOBENZONE 3 g/100 mL; HOMOSALATE 10 g/100 mL; OCTISALATE 5 g/100 mL; OCTOCRYLENE 7 g/100 mL
INACTIVE INGREDIENTS: ARACHIDYL ALCOHOL; DOCOSANOL; SHEA BUTTER; GREEN TEA LEAF; DIPROPYLENE GLYCOL; POLYOXYL 40 HYDROGENATED CASTOR OIL; PHENOXYETHANOL; SILICON DIOXIDE; LEVOMENOL; ARGININE; BUTYLENE GLYCOL; PHENYLETHYL ALCOHOL; ROYAL JELLY; TRIDECETH-9; COCOA; ARACHIDYL GLUCOSIDE; BENZYL ALCOHOL; EDETATE DISODIUM; GLYCERIN; LAUROYL LYSINE; MALTODEXTRIN; ALLANTOIN; ALUMINUM STARCH OCTENYLSUCCINATE; PEG-100 STEARATE; GINGER; HYDROGENATED SOYBEAN LECITHIN; STYRENE/ACRYLAMIDE COPOLYMER (500000 MW); CHLORPHENESIN; CYCLOMETHICONE 5; ETHYLHEXYLGLYCERIN; GLYCERYL MONOSTEARATE; LECITHIN, SOYBEAN

Cover Me Sunscreen SPF 30

Active ingredients Purpose
Avobenzone 3%................Sunscreen
Homosalate 10%...............Sunscreen
Octisalate 5%....................Sunscreen
Octocrylene 7%.................Sunscreen

Uses

- Helps prevent sunburn
- If used as directed with other sun protection measures (see Directions), decreases the risk of skin cancer and early skin aging caused by the sun

Keep out of reach of children. If product is swallowed, get medical help or contact a Poison Control Center right away.

Stop use and ask a doctor if rash occurs

Warnings
For external use only.
Do not use on damaged or broken
skin
When using this product keep out
of eyes. Rinse with water to remove.

Directions:

- apply liberally 15 minutes before sun exposure
- use a water resistant sunscreen if swimming or sweating
- reapply at least every 2 hours
- children under 6 months: Ask a doctor

Sun Protection Measures.
Spending time in the sun increases your risk of skin cancer and early skin aging. To decrease this risk, regularly use a sunscreen with a Broad Spectrum SPF value of 15 or higher and other sun protection measures including:

- limit time in the sun, especially from 10 a.m. - 2 p.m.
- wear long-sleeve shirts, pants, hats, and sunglasses

Inactive ingredients
Acrylates/C10-30 Alkyl Acrylate Crosspolymer, Acrylates/Dimethicone Copolymer, Allantoin, Aluminum Starch Octenylsuccinate, Arachidyl Alcohol, Arachidyl Glucoside, Arginine, Behenyl Alcohol, Benzyl Alcohol, Bisabolol, Butylene Glycol, Butyrospermum Parkii (Shea) Butter, Camellia sinensis Leaf Extract, Chlorphenesin, Cyclopentasiloxane, Dipropylene Glycol, Disodium EDTA, Ethylhexylglycerin, Fragrance/Parfum, Glycerin, Glyceryl Stearate, Hydrogenated Lecithin, Lauroyl Lysine, Lecithin, Maltodextrin, PEG-100 Stearate, PEG-40 Hydrogenated Castor Oil, Phenethyl Alcohol, Phenoxyethanol, Royal Jelly Powder, Royal Jelly, Silica, Styrene/Acrylates Copolymer, Tetrapeptide-45, Trideceth-9, Theobroma Cacao (Cocoa) Seed Extract, Water/Aqua, Zingiber Officinale (Ginger) Root Extract.

PACKAGE LABEL

Jafra Royal Boost

Cover Me Sunscreen Broad Spectrum SPF 30